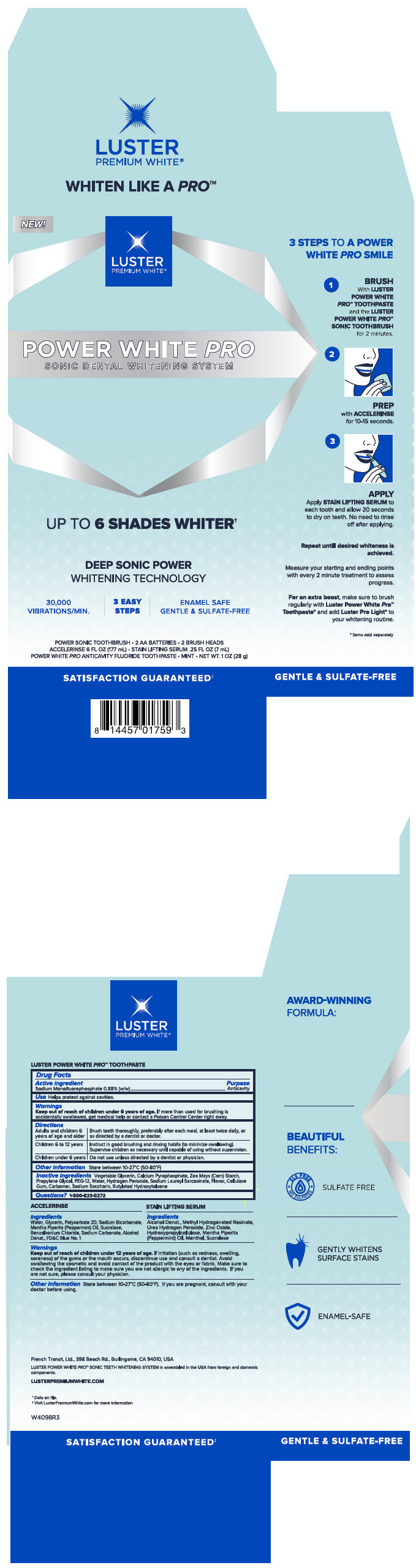 DRUG LABEL: Luster Premium White 
NDC: 72805-160 | Form: KIT | Route: DENTAL
Manufacturer: French Transit, Ltd.
Category: otc | Type: HUMAN OTC DRUG LABEL
Date: 20220112

ACTIVE INGREDIENTS: Sodium Monofluorophosphate 0.88 g/100 g
INACTIVE INGREDIENTS: Water; Calcium Pyrophosphate; Starch, Corn; Propylene Glycol; Polyethylene Glycol 600; Hydrogen Peroxide; Sodium Lauroyl Sarcosinate; Carboxymethylcellulose Sodium, Unspecified; Carbomer Homopolymer Type A (Allyl Pentaerythritol Crosslinked); Saccharin Sodium; Butylated Hydroxytoluene

Luster Premium White®
Pro Sonic Dental Whitening System

Drug Facts

Active Ingredients

Sodium Monofluorophosphate 0.88% (w/w)

Purpose

Anticavity

Use

Helps protect against cavities.

Warnings

Keep out of reach of children under 6 years of age. If more than used for brushing is accidentally swallowed, get medical help or contact a Poison Control Center right away.

Directions

Adults and children 6 years of age and older

Brush teeth thoroughly, preferably after each meal, at least twice daily, or as directed by a dentist or doctor.

Children 6 to 12 years

Instruct in good brushing and rinsing habits (to minimize swallowing). Supervise children as necessary until capable of using without supervision.

Children under 6 years

Do not use unless directed by a dentist or physician

Other information

Store between 10-27° C (50-80° F)

Inactive ingredients

Vegetable Glycerin, Calcium Pyrophosphate, Zea Mays (Corn) Starch, Propylene Glycol, PEG-12, Water, Hydrogen Peroxide, Sodium Lauroyl, Sarcosinate, Flavor, Cellulose Gum, Carbomer, Sodium Saccharin, Butylated Hydroxytoluene

Questions?

1-800-823-5272

PRINCIPAL DISPLAY PANEL - Kit Carton

NEW!

LUSTER
PREMIUM WHITE®

POWER WHITE PRO
SONIC DENTAL WHITENING SYSTEM

UP TO 6 SHADES WHITER†

DEEP SONIC POWER
WHITENING TECHNOLOGY

30,000
VIBRATIONS/MIN.

3 EASY
STEPS

ENAMEL SAFE
GENTLE & SULFATE-FREE

POWER SONIC TOOTHBRUSH • 2 AA BATTERIES • 2 BRUSH HEADS
ACCELERINSE 6 FL OZ (177 mL) • STAIN LIFTING SERUM .25 FL OZ (7 mL)
POWER WHITE PRO ANTICAVITY FLUORIDE TOOTHPASTE • MINT • NET WT. 1 OZ (28 g)

SATISFACTION GUARANTEED‡